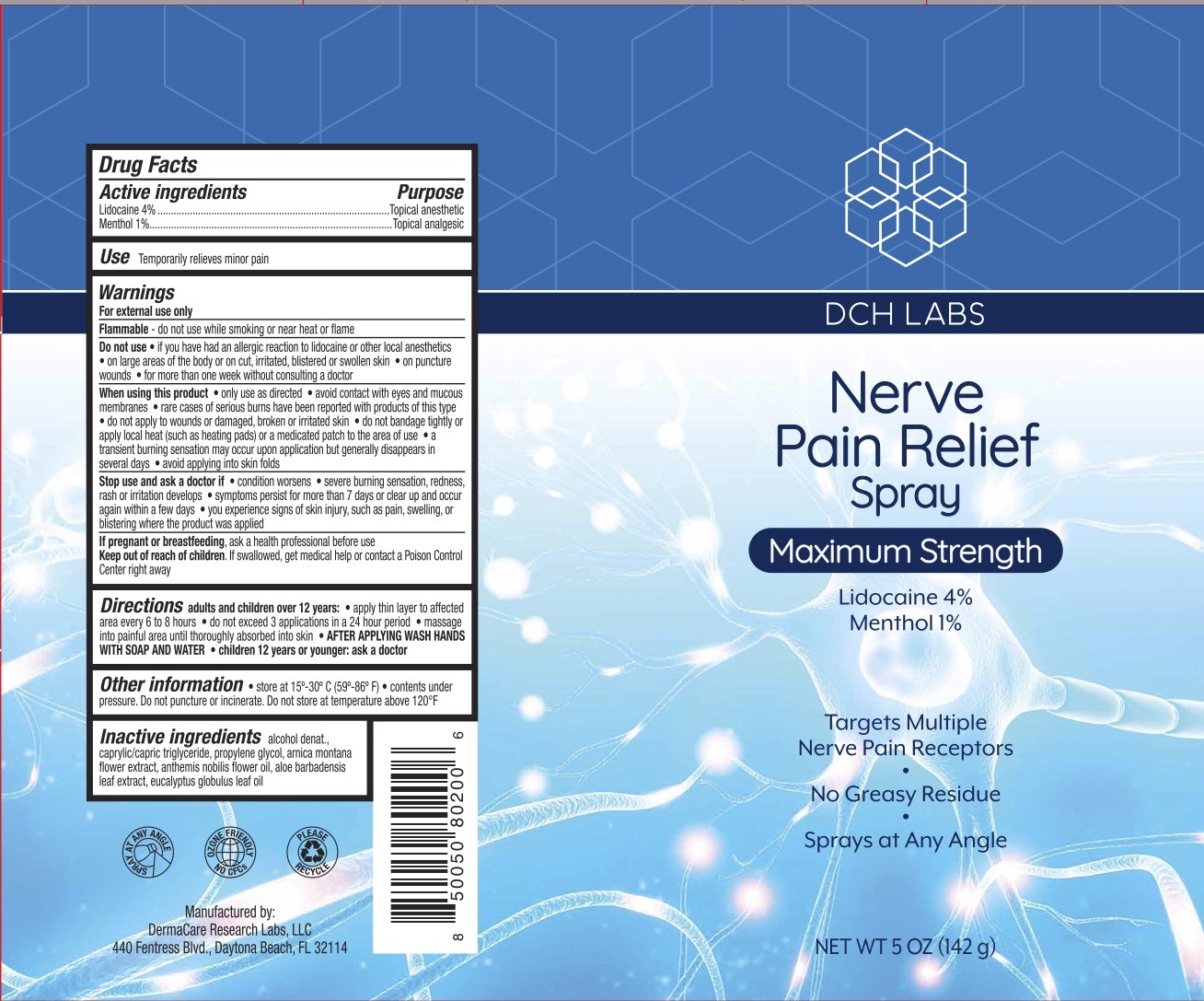 DRUG LABEL: DCH Nerve Pain Relief
NDC: 72839-223 | Form: SPRAY
Manufacturer: Derma Care Research Labs, LLC
Category: otc | Type: HUMAN OTC DRUG LABEL
Date: 20241219

ACTIVE INGREDIENTS: LIDOCAINE 4 g/100 g; MENTHOL 1 g/100 g
INACTIVE INGREDIENTS: ARNICA MONTANA FLOWER; PROPYLENE GLYCOL; ALCOHOL; CHAMAEMELUM NOBILE FLOWER; EUCALYPTUS OIL; ALOE VERA LEAF; MEDIUM-CHAIN TRIGLYCERIDES

DCH Nerve Pain Relief Spray, Lidocaine 4%, Menthol 1%

ACTIVE INGREDIENT

Lidocaine 4%, Menthol 1%

PURPOSE

Topical anesthetic, Topical analgesic

INDICATIONS AND USAGE

Temporarily relieves minor pain

WARNINGS

For external use only.

Flammable--Keep away from fire or flame.

Do not use if you have had an allergic reaction to lidocaine or other local anesthetics, on large areas of he body or on cut, irritated, blistered or swollen skin, on puncture wounds, for more than one week without consulting a doctor.

When using this product only use as directed, avoid contact with eyes and mucous membranes, rare cases of serious burns have been reported with products of this type, do not apply to wounds or damaged, broken, or irritated skin, do not bandage tightly or apply local heat (such as heating pads) or a medicated path to the area of use, a transient burning sensation may occur upon application but generally disappears in several days, avoid applying into skin folds.

Stop use and ask a doctor if condition worsens, severe burning sensation, redness, rash or irritation develops, symptoms persist for more than 7 days or clear up and occur again within a few days, you experience signs of skin injury, such as pain, swelling, or blistering where the product was applied.

.

KEEP OUT OF REACH OF CHILDREN

If swallowed, get medical help or contact a Poison Control Center right away.

DOSAGE AND ADMINISTRATION

When practical, cleanse the affected area with mild soap and warm water, Rinse thoroughly and gently pat dry. Spray affected area. Wash hands after applying. Adults and children 2 years of age and older, apply externally to the affected area up to 6 times a day. Children under 12 years of age: consult a doctor.

INACTIVE INGREDIENT

Alcohol denat., caprylic/capric triglyceride, propylene glycol, arnica montana flower extract, anthemis nobilis flower oil, aloe barbadensis leaf extract, eucalyptus globulus leaf oil.